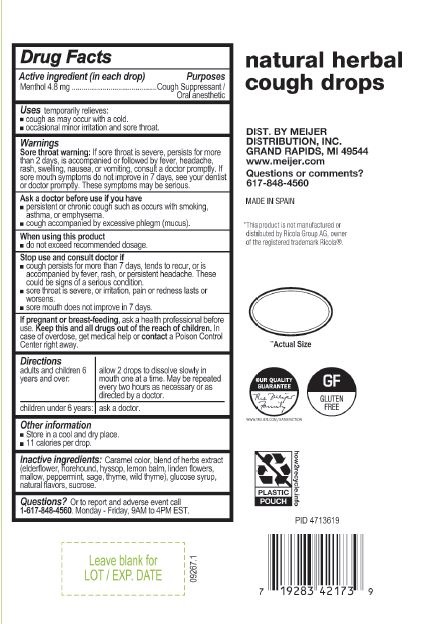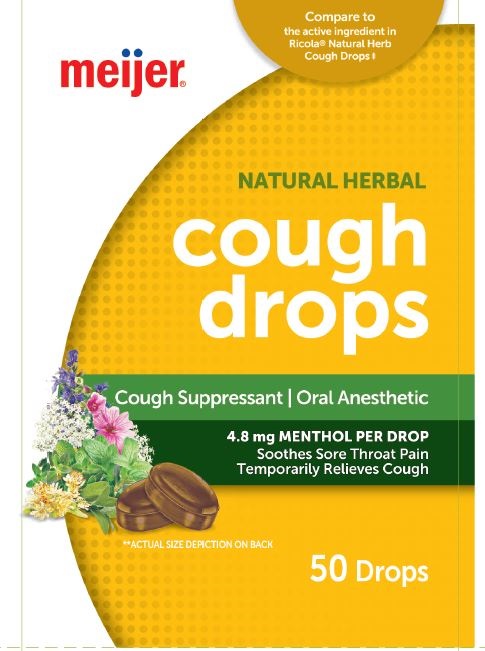 DRUG LABEL: Natural Herbal Cough Drops
NDC: 72628-107 | Form: PASTILLE
Manufacturer: BOSTON NUTRACEUTICAL PRODUCTION, S.L
Category: otc | Type: HUMAN OTC DRUG LABEL
Date: 20241007

ACTIVE INGREDIENTS: MENTHOL 4.8 mg/1 1
INACTIVE INGREDIENTS: HYSSOPUS OFFICINALIS FLOWERING TOP; CARAMEL; HOREHOUND; SUCROSE; SAMBUCUS NIGRA FLOWER; CORN SYRUP; LEMON BALM OIL; MALVA SYLVESTRIS LEAF; PEPPERMINT; TILIA CORDATA FLOWER; SAGE; THYME; WILD THYME

Natural Herbal Cough Drops
Cough Suppressant
Oral Anesthetic

Active Ingredient in each drop Purposes

Menthol 4.8 mg

Cough Suppressant

Oral Anesthetic

Purposes

Temporarily relieves :

- cough as may occur with a cold
- occasional minor irritation and sore throat

Purposes

Temporarily relieves :

- cough as may occur with a cold
- occasional minor irritation and sore throat

Warnings

Sore throat warning: is sore throat is severe, persist for more than 2 days, is accompanied or followed by fever headache, rash, swelling, nausea and vomiting maybe serious consult a doctor promptly. If sore mouth symptons do not improve in 7 days, see your dentist or doctor promptly. These symptons may be serious

Ask a doctor before use if you have

- Persistent or chronic cough such as occurs with smoking, asthma or ephysema.
- Cough accompanied by excessive pleghm (mucus)

Stop use and consult doctor if

- cough persist for more than 7 days or tends to recur or is accompanied by fever, rash or persistent headache. These could be signs of a serious conditions
- sore throat is severe or irritation, pain or redness lasts or worsens.
- sore mouth does not improve in 7 days

PREGNANCY OR BREAST FEEDING

If pregnant or breast-feeding, ask a health professional before use.

KEEP OUT OF REACH OF CHILDREN

Keep this and all drugs out of the reach of children.

OVERDOSAGE

In case of accidental overdose, get medical help or contact a Poison Control Center right away.

Directions

- Adults and children 6 years and over: allow 2 drops to dissolve slowly in mouth one at a time. Maybe repeated every two hours as needed or as directed by a doctor.
- Children under 6 years ask a doctor

Other information

- Store in a cool and dry place
- 11 calories per drop

INACTIVE INGREDIENT

corn syrup, sucrose, caramel color, elderflower, honehound, hyssop, lemon balm, liden fiwer, malow, peppermint, sage, thyme, wild thyme, natural flavours

Questions or to report an adverse event call:

1 617-848-4560

Monday to Friday: 9:00 am to 4:00 pm ET